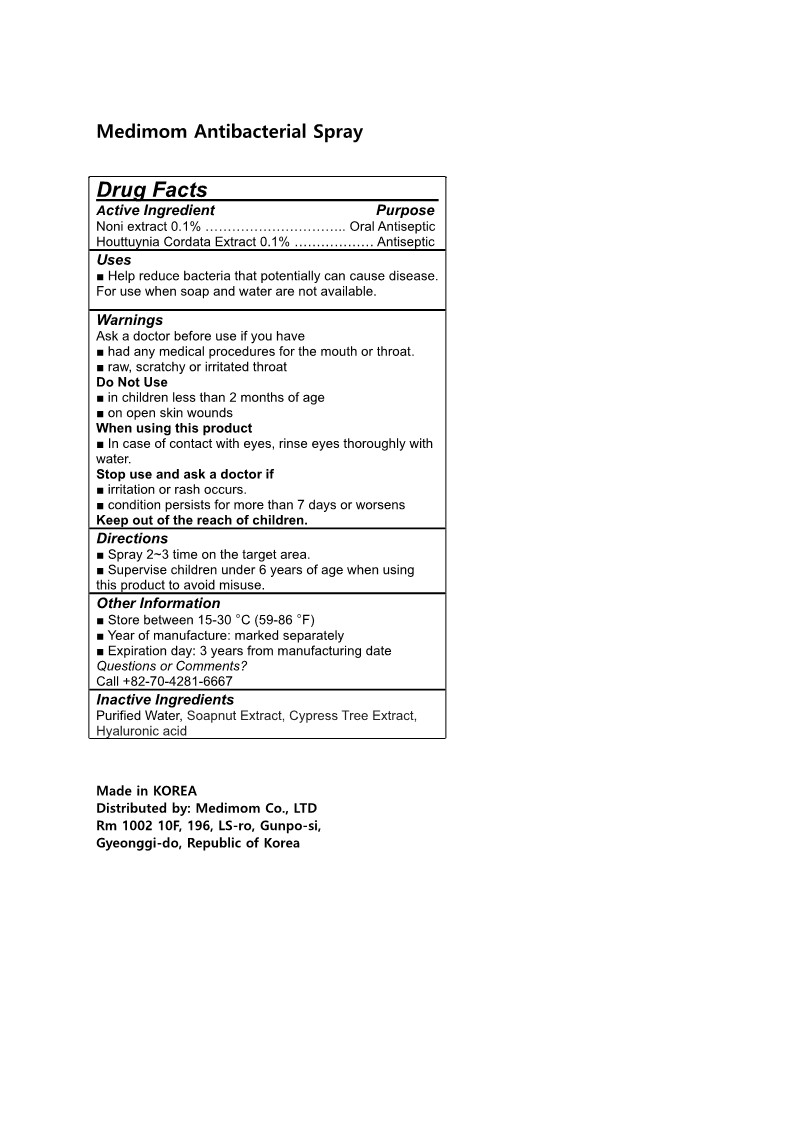 DRUG LABEL: Medimom AntibacterialSpray
NDC: 82380-202 | Form: SPRAY
Manufacturer: Medimom Inc.
Category: otc | Type: HUMAN OTC DRUG LABEL
Date: 20231211

ACTIVE INGREDIENTS: HOUTTUYNIA CORDATA FLOWERING TOP 0.1 g/100 mL; MORINDA CITRIFOLIA LEAF 0.1 g/100 mL
INACTIVE INGREDIENTS: CUPRESSUS SEMPERVIRENS LEAF OIL; SAPINDUS MUKOROSSI FRUIT; WATER; HYALURONIC ACID

82380-202 Medimom Antibacterial Spray

PURPOSE

oral antiseptic, antiseptic

Uses

■ Help reduce bacteria that potentially can cause disease. For use when soap and water are not available.

Active Ingredient

Noni extract 0.1%................................... Oral Antiseptic

Houttuynia Cordata Extract 0.1%........... Antiseptic

Warnings

Ask a doctor before use if you have

■ had any medical procedures for the mouth or throat.

■ raw, scratchy or irritated throat

Warnings

■ Keep out of reach of children.

when using

■ When using the product, in case of contact with eyes, rinse eyes thoroughly with water.

■ Stop use and ask a doctor if you notice the following

Symptoms:

1)Signs of irritation or rash
2)Signs of irritation or rash after exposure to sunlight

Warnings

Do Not Use

■ in children less than 2 months of age

■ on open skin wounds

Inactive Ingredients

Purified Water, Soapnut Extract, Cypress Tree Extract, Hyaluronic acid

Directions

■ Spray 2~3 time on the target area.
■ Supervise children under 6 years of age when using this product to avoid misuse.

Other Information

■ Store between 15-30 °C (59-86 °F)
■ Year of manufacture: marked separately
■ Expiration day: 3 years from manufacturing date Questions or Comments?
Call +82-70-4281-6667